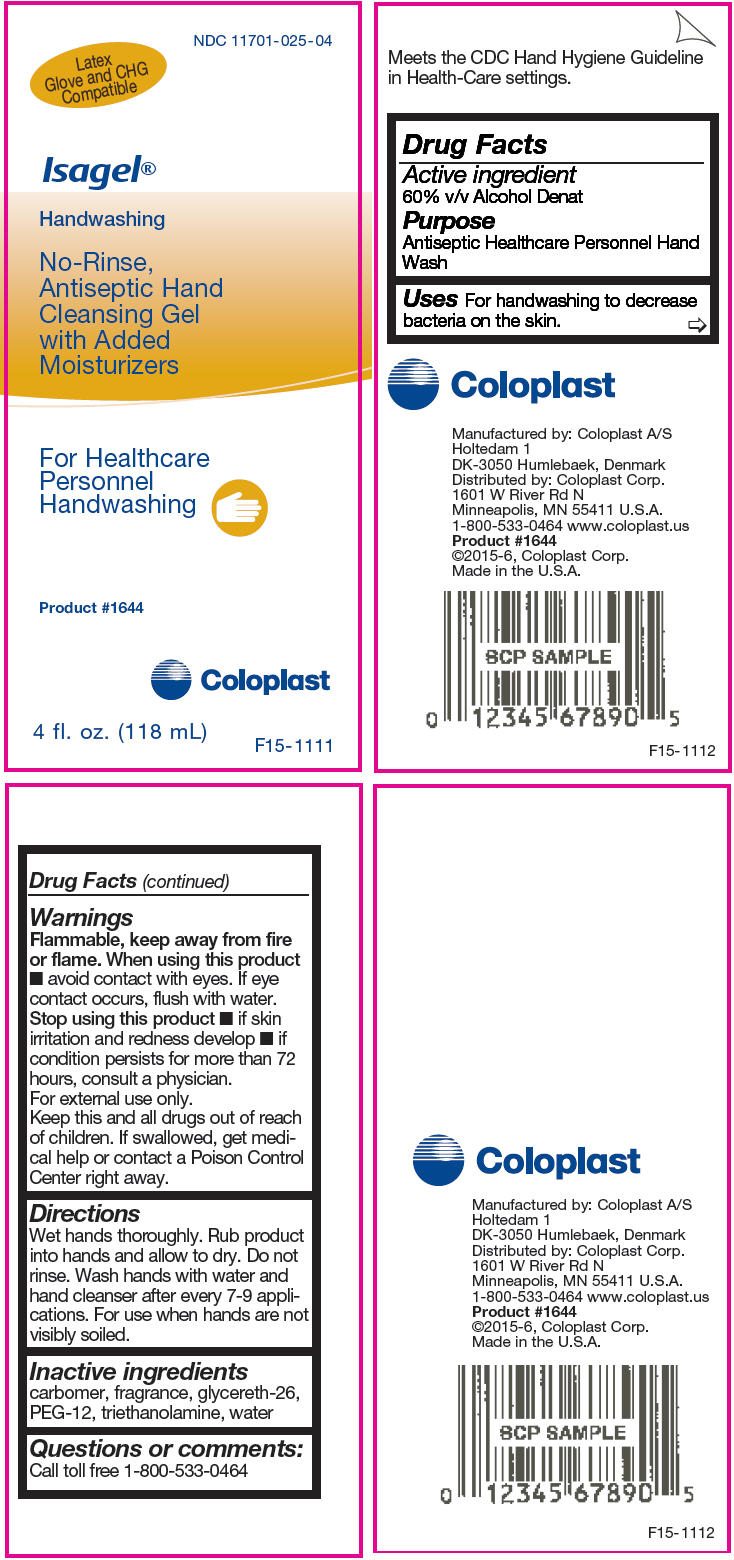 DRUG LABEL: Isagel
NDC: 11701-025 | Form: GEL
Manufacturer: Coloplast Manufacturing US, LLC
Category: otc | Type: HUMAN OTC DRUG LABEL
Date: 20260227

ACTIVE INGREDIENTS: Alcohol 600 mL/1000 mL
INACTIVE INGREDIENTS: TROLAMINE; CARBOMER HOMOPOLYMER TYPE C (ALLYL PENTAERYTHRITOL CROSSLINKED); GLYCERETH-26; POLYETHYLENE GLYCOL 600; WATER

ISAGEL®

Drug Facts

Active ingredient

60% v/v Alcohol Denat

Purpose

Antiseptic Healthcare Personnel Hand Wash

Uses

For handwashing to decrease bacteria on the skin.

Warnings

Flammable, keep away from fire or flame.

When using this product

- avoid contact with eyes. If eye contact occurs, flush with water.

Stop using this product

- if skin irritation and redness develop
- if condition persists for more than 72 hours, consult a physician.

For external use only.

KEEP OUT OF REACH OF CHILDREN

Keep this and all drugs out of reach of children. If swallowed, get medical help or contact a Poison Control Center right away.

Directions

Wet hands thoroughly. Rub product into hands and allow to dry. Do not rinse. Wash hands with water and hand cleanser after every 7-9 applications. For use when hands are not visibly soiled.

Inactive ingredients

carbomer, fragrance, glycereth-26, PEG-12, triethanolamine, water

Questions or comments

Call toll free 1-800-533-0464

Manufactured by: Coloplast A/S
Holtedam 1
DK-3050 Humlebaek, Denmark
Distributed by: Coloplast Corp.
1601 W River Rd N
Minneapolis, MN 55411 U.S.A.

PRINCIPAL DISPLAY PANEL - 118 mL Bottle Label

NDC 11701-025-04

Latex
Glove and CHG
Compatible

Isagel®

Handwashing

No-Rinse,
Antiseptic Hand
Cleansing Gel
with Added
Moisturizers

For Healthcare
Personnel
Handwashing

Product #1644

Coloplast

4 fl. oz. (118 mL)

F15-1111